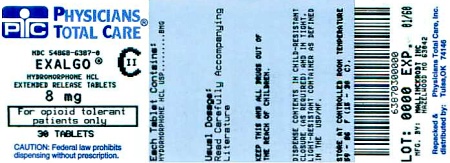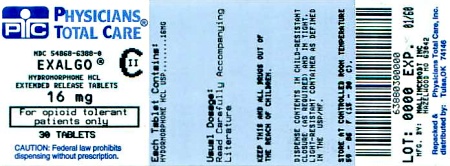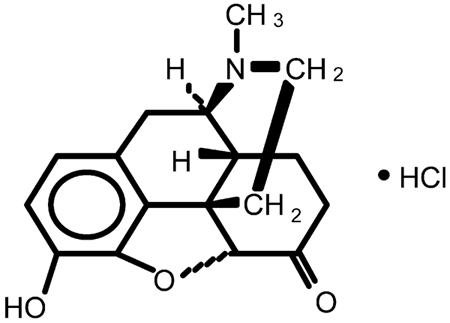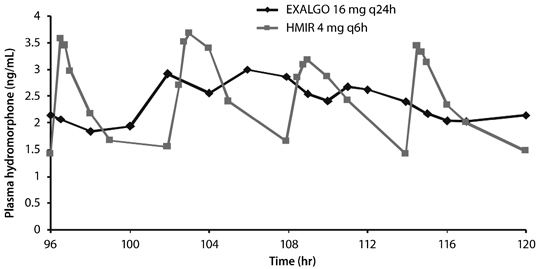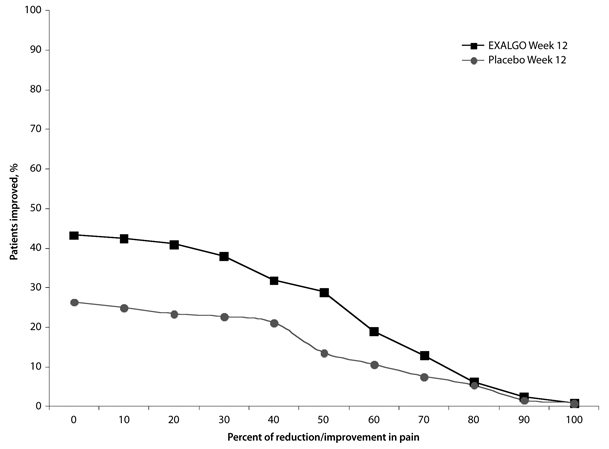 DRUG LABEL: EXALGO
NDC: 54868-6387 | Form: TABLET, EXTENDED RELEASE
Manufacturer: Physicians Total Care, Inc.
Category: prescription | Type: HUMAN PRESCRIPTION DRUG LABEL
Date: 20130128
DEA Schedule: CII

ACTIVE INGREDIENTS: HYDROMORPHONE HYDROCHLORIDE 8 mg/1 1
INACTIVE INGREDIENTS: BUTYLATED HYDROXYTOLUENE; CELLULOSE ACETATE; FERROSOFERRIC OXIDE; FERRIC OXIDE RED; HYPROMELLOSE 2910 (5 MPA.S); ANHYDROUS LACTOSE; LACTOSE MONOHYDRATE; MAGNESIUM STEARATE; POLYETHYLENE GLYCOLS; POVIDONES; SODIUM CHLORIDE; TITANIUM DIOXIDE; TRIACETIN

HIGHLIGHTS OF PRESCRIBING INFORMATION

These highlights do not include all the information needed to use EXALGO® safely and effectively. See full prescribing information for EXALGO.
EXALGO (hydromorphone HCl) Extended-Release Tablets,
for oral use, CII
Initial U.S. Approval: 1984

WARNING: ABUSE POTENTIAL, LIFE-THREATENING RESPIRATORY DEPRESSION, and ACCIDENTAL EXPOSURE

See full prescribing information for complete boxed warning.

- EXALGO contains hydromorphone, a Schedule II controlled substance. Monitor for signs of misuse, abuse, and addiction during EXALGO therapy. (5.1, 9)
- Fatal respiratory depression may occur, with highest risk at initiation and with dose increases; instruct patients on proper administration of EXALGO tablets to reduce risk. EXALGO is for use in opioid-tolerant patients only. Crushing, dissolving, or chewing the tablet can cause rapid release and absorption of a potentially fatal dose of hydromorphone. (5.2)
- Accidental ingestion of EXALGO can result in fatal overdose of hydromorphone, especially in children. (5.3)

RECENT MAJOR CHANGES

Boxed Warning 08/2012

Indications and Usage (1) 08/2012

Dosage and Administration (2) 08/2012

Contraindications (4) 08/2012

Warnings and Precautions (5) 08/2012

1 INDICATIONS AND USAGE

EXALGO is an opioid agonist indicated for the management of moderate to severe pain in opioid tolerant patients requiring continuous, around-the-clock opioid analgesia for an extended period of time (1).

Limitations of Use

- EXALGO is not for use:
  - As an as-needed (prn) analgesic (1)
  - For pain that is mild or not expected to persist for an extended period of time (1)
  - For acute pain (1)
  - For postoperative pain, unless the patient is already receiving chronic opioid therapy prior to surgery, or if the postoperative pain is expected to be moderate to severe and persist for an extended period of time (1)

EXALGO is only for patients in whom tolerance to an opioid of comparable potency is established. (1)

2 DOSAGE AND ADMINISTRATION

- Individualize dosing based on patient’s prior analgesic treatment experience, and titrate as needed to provide adequate analgesia and minimize adverse reactions. (2.1, 2.2, 2.3)
- For once daily administration (2.1)
- Instruct patients to swallow EXALGO tablets intact. (2.6)
- Do not abruptly discontinue EXALGO. (2.3, 5.12)

3 DOSAGE FORMS AND STRENGTHS

- Tablets (hydromorphone): 8 mg, 12 mg, 16 mg, 32 mg (3)

4 CONTRAINDICATIONS

- Opioid non-tolerant patients (4)
- Significant respiratory depression (4)
- Acute or severe bronchial asthma (4)
- Known or suspected paralytic ileus (4)
- Narrowed or obstructed gastrointestinal tract (4)
- Known hypersensitivity to any components including hydromorphone hydrochloride and sulfites (4, 5.10)

5 WARNINGS AND PRECAUTIONS

- Elderly, cachectic, and debilitated patients, and patients with chronic pulmonary disease: Monitor closely because of increased risk of respiratory depression. (5.4, 5.5)
- Interaction with CNS depressants: Consider dose reduction of one or both drugs because of additive effects. (5.6, 7.1)
- Hypotensive effect: Monitor during dose initiation and titration (5.7)
- Patients with head injury or increased intracranial pressure: Monitor for sedation and respiratory depression. Avoid use of EXALGO in patients with impaired consciousness or coma susceptible to intracranial effects of CO2 retention. (5.8)

6 ADVERSE REACTIONS

Most common adverse reactions (>10%) are: constipation, nausea, vomiting, somnolence, headache, and dizziness (6.1).

To report SUSPECTED ADVERSE REACTIONS, contact Mallinckrodt at 1-800-778-7898 or FDA at 1-800-FDA-1088 or www.fda.gov/medwatch.

7 DRUG INTERACTIONS

- Mixed agonist/antagonist opioid analgesics: Avoid use with EXALGO because they may reduce analgesic effect of EXALGO or precipitate withdrawal symptoms. (5.12, 7.2)
- CNS depressants: Avoid use of EXALGO with other drugs or substances having increased risk of respiratory depression. (7.1)
- Monoamine oxidase inhibitors (MAOIs): Avoid EXALGO in patients taking MAOIs or within 14 days of stopping such treatment. (7.3)

8 USE IN SPECIFIC POPULATIONS

- Pregnancy: EXALGO is not recommended. Based on animal data, may cause fetal harm. (8.1)
- Nursing mothers: EXALGO is not recommended. Hydromorphone has been detected in human milk. Closely monitor infants of nursing women receiving EXALGO. (8.3)
- Hepatic or renal impairment: Administer a reduced dose of EXALGO in patients with moderate hepatic (8.7) and moderate renal impairment (8.8). Consider use of an alternate analgesic in patients with severe hepatic (8.7) and renal impairment. (8.8)

FULL PRESCRIBING INFORMATION

WARNING: ABUSE POTENTIAL, LIFE-THREATENING RESPIRATORY DEPRESSION, and ACCIDENTAL EXPOSURE

Abuse Potential

EXALGO contains hydromorphone, an opioid agonist and a Schedule II controlled substance with an abuse liability similar to other opioid agonists, legal or illicit [see Warnings and Precautions (5.1)]. Assess each patient’s risk for opioid abuse or addiction prior to prescribing EXALGO. The risk for opioid abuse is increased in patients with a personal or family history of substance abuse (including drug or alcohol abuse or addiction) or mental illness (e.g., major depressive disorder). Routinely monitor all patients receiving EXALGO for signs of misuse, abuse, and addiction during treatment [see Drug Abuse and Dependence (9)].

Life-threatening Respiratory Depression

Respiratory depression, including fatal cases, may occur with use of EXALGO, even when the drug has been used as recommended and not misused or abused [see Warnings and Precautions (5.2)]. EXALGO is for use in opioid tolerant patients only. Proper dosing and titration are essential and EXALGO should be prescribed only by healthcare professionals who are knowledgeable in the use of potent opioids for the management of chronic pain. Monitor for respiratory depression, especially during initiation of EXALGO or following a dose increase. Crushing, dissolving, or chewing the tablet can cause rapid release and absorption of a potentially fatal dose of hydromorphone.

Accidental Exposure

Accidental ingestion of EXALGO, especially in children, can result in a fatal overdose of hydromorphone [see Warnings and Precautions (5.3)].

1 INDICATIONS AND USAGE

EXALGO is indicated for the management of moderate to severe pain in opioid tolerant patients requiring continuous, around-the-clock opioid analgesia for an extended period of time.

Patients considered opioid tolerant are those who are taking at least 60 mg oral morphine per day, 25 mcg transdermal fentanyl/hour, 30 mg oral oxycodone/day, 8 mg oral hydromorphone/day, 25 mg oral oxymorphone/day or an equianalgesic dose of another opioid, for a week or longer.

Limitations of Use

EXALGO is not for use:

- As an as-needed (prn) analgesic
- For pain that is mild or not expected to persist for an extended period of time
- For acute pain
- For postoperative pain.

2 DOSAGE AND ADMINISTRATION

2.1 Initial Dosing

Initiate the dosing regimen for each patient individually, taking into account the patient's prior analgesic treatment experience. Overestimating the EXALGO dose when converting patients from another opioid medication can result in fatal overdose with the first dose. Monitor patients closely for respiratory depression, especially within the first 24 to 72 hours of initiating therapy with EXALGO [see Warnings and Precautions (5.2)].

Consider the following factors when selecting an initial dose of EXALGO:

- Total daily dose and potency of the opioid the patient has been taking previously;
- Reliability of the relative potency estimate used to calculate the equivalent dose of hydromorphone needed (Note: potency estimates may vary with the route of administration);
- Patient's degree of opioid experience and opioid tolerance;
- General condition and medical status of the patient;
- Concurrent medication;
- Type and severity of the patient's pain.

EXALGO is administered at a frequency of once daily (every 24 hours), approximately the same time every day, with or without food.

To avoid medication errors, prescribers and pharmacists must be aware that hydromorphone is available as both immediate-release 8 mg tablets and extended-release 8 mg tablets.

Discontinue or taper all other extended-release opioids when beginning EXALGO therapy. As EXALGO is only for use in opioid-tolerant patients, do not begin any patient on EXALGO as the first opioid.

Conversion from Other Oral Hydromorphone Formulations to EXALGO

Patients receiving oral immediate-release hydromorphone may be converted to EXALGO by administering a starting dose equivalent to the patient’s total daily oral hydromorphone dose, taken once daily.

Conversion from Oral Opioids to EXALGO

While there are useful tables of oral and parenteral equivalents, there is substantial inter-patient variation in the relative potency of different opioid drugs and formulations. Specific recommendations of equianalgesic doses are not available because of a lack of systematic evidence for these types of analgesic substitutions. Published relative potency data are available, but such ratios are approximations. As such, it is safer to underestimate a patient's 24-hour oral hydromorphone requirement and provide rescue medication (e.g. immediate-release hydromorphone) than to overestimate and manage an adverse reaction.

The following table was used in a clinical trial of EXALGO. The recommended starting dose of EXALGO is 50% of the calculated estimate of daily hydromorphone requirement. Calculate the estimated daily hydromorphone requirement using Table 1.

- The conversion ratios in this Table 1 are only to be used for the conversion from current oral opioid therapy to EXALGO. Do not use this table to convert patients from EXALGO to another opioid. Doing so may result in fatal overdose.
- For patients on a single opioid, sum the total daily dose of the opioid and then multiply the total daily dose by the conversion ratio to calculate the approximate oral hydromorphone equivalent.
- For patients on a regimen of mixed opioids, calculate the approximate oral hydromorphone dose for each opioid and sum the totals.
- For patients on a regimen of fixed-ratio opioid/non-opioid analgesic medications, only the opioid component of these medications should be used in the conversion.
- It is extremely important to monitor all patients closely when converting from methadone to other opioid agonists. The ratio between methadone and other opioid agonists may vary widely as a function of previous dose exposure. Methadone has a long half-life and tends to accumulate in the plasma.
- Monitor patients for signs or symptoms of opioid withdrawal when converting patients to EXALGO.

Example conversion from a single opioid to EXALGO:

Step 1: Sum the total daily dose of the opioid

- 30 mg of oxycodone twice daily equals a total daily dose of 60 mg of oxycodone

Step 2: Calculate the approximately equivalent dose of oral hydromorphone based on the total daily dose of the opioid

- Multiply the 60 mg total daily dose of oxycodone by the conversion factor of 0.4 for a result of 24 mg of oral hydromorphone

Step 3: Calculate the starting dose of EXALGO, which is 50% of the calculated oral hydromorphone dose

- 50% of 24 mg results in an initial dose of 12 mg of EXALGO once daily
- Adjust individually for each patient

Table 1.
Conversion Ratios to EXALGO*

Previous Opioid | Approximate Equivalent; Oral Dose | Approximate Oral; Conversion Ratio
Hydromorphone | 12 mg | 1
Codeine | 200 mg | 0.06
Hydrocodone | 30 mg | 0.4
Methadone† | 20 mg | 0.6
Morphine | 60 mg | 0.2
Oxycodone | 30 mg | 0.4
Oxymorphone | 20 mg | 0.6

* The conversion ratios and approximate equivalent doses in this conversion table are only to be used for the conversion from current opioid therapy to EXALGO.

† It is extremely important to monitor all patients closely when converting from methadone to other opioid agonists. The ratio between methadone and other opioid agonists may vary widely as a function of previous dose exposure. Methadone has a long half-life and tends to accumulate in the plasma.

Conversion from Transdermal Fentanyl to EXALGO

Eighteen hours following the removal of the transdermal fentanyl patch, EXALGO treatment can be initiated. For each 25 mcg/hr fentanyl transdermal dose, the equianalgesic dose of EXALGO is 12 mg every 24 hours. An appropriate starting dose of EXALGO is 50% of the calculated total daily dose every 24 hours.

2.2 Titration and Maintenance of Therapy

Individually titrate EXALGO to a dose that provides adequate analgesia and minimizes adverse reactions. Continually reevaluate patients receiving EXALGO to assess the maintenance of pain control and the relative incidence of adverse reactions. During chronic therapy, especially for non-cancer-related pain (or pain associated with other terminal illnesses), periodically reassess the continued need for the use of opioid analgesics.

If the level of pain increases, attempt to identify the source of increased pain, while adjusting the EXALGO dose to decrease the level of pain. Plasma levels of EXALGO are sustained for 18 to 24 hours. Dosage adjustments may be made every 3 to 4 days. Patients who experience breakthrough pain may require dosage adjustment or rescue medication.

If signs of excessive opioid-related adverse reactions are observed, the next dose may be reduced. Adjust the dose to obtain an appropriate balance between management of pain and opioid-related adverse reactions.

2.3 Discontinuation of EXALGO

When a patient no longer requires therapy with EXALGO, taper doses gradually, by 25% to 50% every 2 or 3 days down to a dose of 8 mg before discontinuation of therapy, to prevent signs and symptoms of withdrawal in the opioid-tolerant patient.

To dispose of unused EXALGO flush all remaining tablets down the toilet or remit to authorities at a certified drug take-back program.

2.4 Hepatic Impairment

Start patients with moderate hepatic impairment on 25% of the EXALGO dose that would be prescribed for patients with normal hepatic function. Closely monitor patients with moderate hepatic impairment for respiratory and central nervous system depression during initiation of therapy with EXALGO and during dose titration. Use of alternate analgesics is recommended for patients with severe hepatic impairment [see Use in Specific Populations (8.7)].

2.5 Renal Impairment

Start patients with moderate renal impairment on 50% and patients with severe renal impairment on 25% of the EXALGO dose that would be prescribed for patients with normal renal function. Closely monitor patients with renal impairment for respiratory and central nervous system depression during initiation of therapy with EXALGO and during dose titration. As EXALGO is only intended for once daily administration, consider use of an alternate analgesic that may permit more flexibility with the dosing interval in patients with severe renal impairment [see Use in Specific Populations (8.8)].

2.6 Administration of EXALGO

Instruct patients to swallow EXALGO tablets intact. The tablets are not to be crushed, dissolved, or chewed due to the risk of rapid release and absorption of a potentially fatal dose of hydromorphone [see Warnings and Precautions (5.2)].

3 DOSAGE FORMS AND STRENGTHS

EXALGO is available in 8 mg, 12 mg, 16 mg or 32 mg dosage strengths. The 8 mg tablets are round, biconvex, red tablets imprinted with "EXH 8" on one side. The 12 mg tablets are round, biconvex, dark yellow tablets imprinted with "EXH 12" on one side. The 16 mg tablets are round, biconvex, yellow tablets imprinted with "EXH 16" on one side. The 32 mg tablets are round, biconvex, white tablets imprinted with “EXH 32” on one side.

4 CONTRAINDICATIONS

EXALGO is contraindicated in:

- Opioid non-tolerant patients. Fatal respiratory depression could occur in patients who are not opioid tolerant.
- Patients with significant respiratory depression
- Patients with acute or severe bronchial asthma in an unmonitored setting or in the absence of resuscitative equipment
- Patients with known or suspected paralytic ileus
- Patients who have had surgical procedures and/or underlying disease resulting in narrowing of the gastrointestinal tract, or have “blind loops” of the gastrointestinal tract or gastrointestinal obstruction.
- Patients with hypersensitivity (e.g., anaphylaxis) to hydromorphone or sulfite-containing medications [see Warnings and Precautions (5.10)]

5 WARNINGS AND PRECAUTIONS

5.1 Abuse Potential

EXALGO contains hydromorphone, an opioid agonist and a Schedule II controlled substance. Hydromorphone can be abused in a manner similar to other opioid agonists, legal or illicit. Opioid agonists are sought by drug abusers and people with addiction disorders and are subject to criminal diversion. Consider these risks when prescribing or dispensing EXALGO in situations where there is concern about increased risks of misuse, abuse, or diversion. Concerns about abuse, addiction, and diversion should not, however, prevent the proper management of pain.

Assess each patient’s risk for opioid abuse or addiction prior to prescribing EXALGO. The risk for opioid abuse is increased in patients with a personal or family history of substance abuse (including drug or alcohol abuse or addiction) or mental illness (e.g., major depression). Patients at increased risk may still be appropriately treated with modified-release opioid formulations; however these patients will require intensive monitoring for signs of misuse, abuse, or addiction. Routinely monitor all patients receiving opioids for signs of misuse, abuse, and addiction because these drugs carry a risk for addiction even under appropriate medical use.

Misuse or abuse of EXALGO by crushing, chewing, snorting, or injecting the dissolved product will result in the uncontrolled delivery of the opioid and pose a significant risk that could result in overdose and death [see Overdosage (10)].

Contact local state professional licensing board or state controlled substances authority for information on how to prevent and detect abuse or diversion of this product.

5.2 Life-threatening Respiratory Depression

Respiratory depression is the primary risk of EXALGO. Respiratory depression, if not immediately recognized and treated, may lead to respiratory arrest and death. Respiratory depression from opioids is manifested by a reduced urge to breathe and a decreased rate of respiration, often associated with a “sighing” pattern of breathing (deep breaths separated by abnormally long pauses). Carbon dioxide (CO2) retention from opioid-induced respiratory depression can exacerbate the sedating effects of opioids. Management of respiratory depression may include close observation, supportive measures, and use of opioid antagonists, depending on the patient’s clinical status [see Overdosage (10)].

While serious, life-threatening, or fatal respiratory depression can occur at any time during the use of EXALGO, the risk is greatest during the initiation of therapy or following a dose increase. Closely monitor patients for respiratory depression when initiating therapy with EXALGO and following dose increases. Instruct patients against use by individuals other than the patient for whom EXALGO was prescribed and to keep EXALGO out of the reach of children, as such inappropriate use may result in fatal respiratory depression.

To reduce the risk of respiratory depression, proper dosing and titration of EXALGO are essential [see Dosage and Administration (2.1, 2.2)]. Overestimating the EXALGO dose when converting patients from another opioid product can result in fatal overdose with the first dose. Respiratory depression has also been reported with use of modified-release opioids when used as recommended and not misused or abused.

To further reduce the risk of respiratory depression, consider the following:

- Proper dosing and titration are essential and EXALGO should be prescribed only by healthcare professionals who are knowledgeable in the use of potent opioids for the management of chronic pain.
- EXALGO is for use in opioid-tolerant patients only. Ingestion of EXALGO may cause fatal respiratory depression when administered to patients not already tolerant to opioids.
- Instruct patients to swallow EXALGO tablets intact. The tablets are not to be crushed, dissolved, or chewed. The resulting hydromorphone dose may be fatal.
- EXALGO is contraindicated in patients with respiratory depression and in patients with conditions that increase the risk of life-threatening respiratory depression [see Contraindications (4)].

5.3 Accidental Exposure

Accidental ingestion of EXALGO, especially in children, can result in a fatal overdose of hydromorphone.

5.4 Elderly, Cachectic, and Debilitated Patients

Respiratory depression is more likely to occur in elderly, cachectic, or debilitated patients as they may have altered pharmacokinetics due to poor fat stores, muscle wasting, or altered clearance compared to younger, healthier patients. Therefore, monitor such patients closely, particularly when initiating and titrating EXALGO and when EXALGO is given concomitantly with other drugs that depress respiration [see Warnings and Precautions (5.2, 5.6)].

5.5 Use in Patients with Chronic Pulmonary Disease

Monitor patients with significant chronic obstructive pulmonary disease or cor pulmonale, and patients having a substantially decreased respiratory reserve, hypoxia, hypercapnia, or pre-existing respiratory depression for respiratory depression, particularly when initiating therapy and titrating with EXALGO, as in these patients, even usual therapeutic doses of EXALGO may decrease respiratory drive to the point of apnea [see Warnings and Precautions (5.2)]. Consider the use of alternative non-opioid analgesics in these patients if possible.

5.6 Interactions with Alcohol, Other CNS Depressants, and Illicit Drugs

Hypotension, profound sedation, coma, or respiratory depression may result if EXALGO is used concomitantly with other CNS depressants (e.g., sedatives, anxiolytics, hypnotics, neuroleptics, other opioids). When considering the use of EXALGO in a patient taking a CNS depressant, assess the duration of use of the CNS depressant and the patient’s response, including the degree of tolerance that has developed to CNS depression. Additionally, consider the patient’s use, if any, of alcohol or illicit drugs that cause CNS depression. If EXALGO therapy is to be initiated in a patient taking a CNS depressant, start with a lower EXALGO dose than usual and monitor patients for signs of sedation and respiratory depression and consider using a lower dose of the concomitant CNS depressant [see Drug Interactions (7.1)].

5.7 Hypotensive Effect

EXALGO may cause severe hypotension including orthostatic hypotension and syncope in ambulatory patients. There is an increased risk in patients whose ability to maintain blood pressure has already been compromised by a reduced blood volume or concurrent administration of certain CNS depressant drugs (e.g. phenothiazines or general anesthetics) [see Drug Interactions (7.1)]. Monitor these patients for signs of hypotension after initiating or titrating the dose of EXALGO.

5.8 Use in Patients with Head Injury or Increased Intracranial Pressure

Monitor patients taking EXALGO who may be susceptible to the intracranial effects of CO2 retention (e.g., those with evidence of increased intracranial pressure or brain tumors) for signs of sedation and respiratory depression, particularly when initiating therapy with EXALGO. EXALGO may reduce respiratory drive, and the resultant CO2 retention can further increase intracranial pressure. Opioids may also obscure the clinical course in a patient with a head injury. Avoid the use of EXALGO in patients with impaired consciousness or coma.

5.9 Use in Patients with Gastrointestinal Conditions

EXALGO is contraindicated in patients with paralytic ileus. Avoid the use of EXALGO in patients with other GI obstruction.

Because the EXALGO tablet is nondeformable and does not appreciably change in shape in the GI tract, EXALGO is contraindicated in patients with preexisting severe gastrointestinal narrowing (pathologic or iatrogenic, for example: esophageal motility disorders, small bowel inflammatory disease, “short gut” syndrome due to adhesions or decreased transit time, past history of peritonitis, cystic fibrosis, chronic intestinal pseudoobstruction, or Meckel’s diverticulum). There have been reports of obstructive symptoms in patients with known strictures or risk of strictures, such as previous GI surgery, in association with the ingestion of drugs in nondeformable extended-release formulations.

It is possible that EXALGO tablets may be visible on abdominal x-rays under certain circumstances, especially when digital enhancing techniques are utilized.

The hydromorphone in EXALGO may cause spasm of the sphincter of Oddi. Monitor patients with biliary tract disease, including acute pancreatitis, for worsening symptoms.

5.10 Sulfites

EXALGO contains sodium metabisulfite, a sulfite that may cause allergic-type reactions including anaphylactic symptoms and life-threatening or less severe asthmatic episodes in certain susceptible people. The overall prevalence of sulfite sensitivity in the general population is unknown and probably low. Sulfite sensitivity is seen more frequently in asthmatic than in nonasthmatic people.

5.11 Use in Patients with Convulsive or Seizure Disorders

The hydromorphone in EXALGO may aggravate convulsions in patients with convulsive disorders, and may induce or aggravate seizures in some clinical settings. Monitor patients with a history of seizure disorders for worsened seizure control during EXALGO therapy.

5.12 Avoidance of Withdrawal

Avoid the use of mixed agonist/antagonist analgesics (i.e., pentazocine, nalbuphine, and butorphanol) in patients who have received or are receiving a course of therapy with a full opioid agonist analgesic, including EXALGO. In these patients, mixed agonists/antagonists analgesics may reduce the analgesic effect and/or may precipitate withdrawal symptoms [see Drug Interactions (7.2)].

When discontinuing EXALGO, gradually taper the dose [see Dosage and Administration (2.3)]. Do not abruptly discontinue EXALGO.

5.13 Driving and Operating Machinery

EXALGO may impair the mental and/or physical abilities needed to perform potentially hazardous activities such as driving a car or operating machinery. Warn patients not to drive or operate dangerous machinery unless they are tolerant to the effects of EXALGO and know how they will react to the medication.

6 ADVERSE REACTIONS

The following serious adverse reactions are discussed elsewhere in the labeling:

- Respiratory Depression [see Warnings and Precautions (5.2)]
- Chronic Pulmonary Disease [see Warnings and Precautions (5.5)]
- Head Injuries and Increased Intracranial Pressure [see Warnings and Precautions (5.8)]
- Interactions with Other CNS Depressants [see Warnings and Precautions (5.6)]
- Hypotensive Effect [see Warnings and Precautions (5.7)]
- Gastrointestinal Effects [see Warnings and Precautions (5.9)]
- Seizures [see Warnings and Precautions (5.11)]

6.1 Clinical Studies Experience

Because clinical trials are conducted under widely varying conditions, adverse reaction rates observed in the clinical trials of a drug cannot be directly compared to rates in the clinical trials of another drug and may not reflect the rates observed in clinical practice.

EXALGO was administered to a total of 2,524 patients in 15 controlled and uncontrolled clinical studies. Of these, 423 patients were exposed to EXALGO for greater than 6 months and 141 exposed for greater than one year.

The most common adverse reactions leading to study discontinuation were nausea, vomiting, constipation, somnolence, and dizziness. The most common treatment-related serious adverse reactions from controlled and uncontrolled chronic pain studies were drug withdrawal syndrome, overdose, confusional state, and constipation.

The overall incidence of adverse reactions in patients greater than 65 years of age was higher, with a greater than 5% difference in rates for constipation and nausea when compared with younger patients. The overall incidence of adverse reactions in female patients was higher, with a greater than 5% difference in rates for nausea, vomiting, constipation and somnolence when compared with male patients.

A 12-week double-blind, placebo-controlled, randomized withdrawal study was conducted in opioid tolerant patients with moderate to severe low back pain [see Clinical Studies (14)]. A total of 447 patients were enrolled into the open-label titration phase with 268 patients randomized into the double-blind treatment phase. The adverse reactions that were reported in at least 2% of the patients are contained in Table 2.

Table 2.

Number (%) of Patients with Adverse Reactions Reported in ≥ 2% of Patients
with Moderate to Severe Low Back Pain During the Open-Label Titration Phase or Double-Blind Treatment Phase by Preferred Term

Preferred Term | Open-Label; Titration Phase | Double-Blind Treatment Phase
 | EXALGO (N=447) | EXALGO (N=134) | Placebo (N=134)
Constipation | 69 (15) | 10 (7) | 5 (4)
Nausea | 53 (12) | 12 (9) | 10 (7)
Somnolence | 39 (9) | 1 (1) | 0 (0)
Headache | 35 (8) | 7 (5) | 10 (7)
Vomiting | 29 (6) | 8 (6) | 6 (4)
Drug Withdrawal Syndrome | 22 (5) | 13 (10) | 16 (12)
Pruritus | 21 (5) | 1 (1) | 0 (0)
Dizziness | 17 (4) | 3 (2) | 2 (1)
Asthenia/Fatigue | 16 (4) | 2 (1) | 6 (4)
Insomnia | 13 (3) | 7 (5) | 5 (4)
Diarrhea | 13 (3) | 5 (4) | 9 (7)
Back Pain | 13 (3) | 6 (4) | 8 (6)
Dry Mouth | 13 (3) | 2 (1) | 0 (0)
Edema Peripheral | 13 (3) | 3 (2) | 1 (1)
Hyperhidrosis | 13 (3) | 2 (1) | 2 (1)
Anorexia/Decreased Appetite | 10 (2) | 2 (1) | 0 (0)
Arthralgia | 9 (2) | 8 (6) | 3 (2)
Anxiety | 9 (2) | 0 (0) | 4 (3)
Abdominal Pain | 9 (2) | 4 (3) | 3 (2)
Muscle Spasms | 5 (1) | 3 (2) | 1 (1)
Weight Decreased | 3 (1) | 4 (3) | 3 (2)

The adverse reactions that were reported in at least 2% of the total treated patients (N=2,474) in the 14 chronic clinical trials are contained in Table 3.

Table 3.

Number (%) of Patients with Adverse Reactions Reported in ≥ 2% of Patients
with Chronic Pain Receiving EXALGO in 14 Clinical Studies by Preferred Term

Preferred Term | All Patients (N=2,474)
Constipation | 765 (31)
Nausea | 684 (28)
Vomiting | 337 (14)
Somnolence | 367 (15)
Headache | 308 (12)
Asthenia/Fatigue | 272 (11)
Dizziness | 262 (11)
Diarrhea | 201 (8)
Pruritus | 193 (8)
Insomnia | 161 (7)
Hyperhidrosis | 143 (6)
Edema Peripheral | 135 (5)
Anorexia/Decreased Appetite | 139 (6)
Dry Mouth | 121 (5)
Abdominal Pain | 115 (5)
Anxiety | 95 (4)
Back Pain | 95 (4)
Dyspepsia* | 88 (4)
Depression | 81 (3)
Dyspnea | 76 (3)
Muscle Spasms | 74 (3)
Arthralgia | 72 (3)
Rash | 64 (3)
Pain in Extremity | 63 (3)
Pain | 58 (2)
Drug Withdrawal Syndrome | 55 (2)
Pyrexia | 52 (2)
Fall | 51 (2)
Chest pain | 51 (2)

* Reflux esophagitis, gastroesophageal reflux disease and Barrett’s esophagus were grouped and reported with dyspepsia

The following Adverse Reactions occurred in patients with an overall frequency of < 2% and are listed in descending order within each System Organ Class:

Cardiac disorders: palpitations, tachycardia, bradycardia, extrasystoles

Ear and labyrinth disorders: vertigo, tinnitus

Endocrine disorders: hypogonadism

Eye disorders: vision blurred, diplopia, dry eye, miosis

Gastrointestinal disorders: flatulence, dysphagia, hematochezia, abdominal distension, hemorrhoids, abnormal feces, intestinal obstruction, eructation, diverticulum, gastrointestinal motility disorder, large intestine perforation, anal fissure, bezoar, duodenitis, ileus, impaired gastric emptying, painful defecation

General disorders and administration site conditions: chills, malaise, feeling abnormal, feeling hot and cold, feeling jittery, hangover, difficulty in walking, feeling drunk, hypothermia

Infections and infestations: gastroenteritis, diverticulitis

Injury, poisoning and procedural complications: contusion, overdose

Investigations: weight decreased, hepatic enzyme increased, blood potassium decreased, blood amylase increased, blood testosterone decreased, oxygen saturation decreased

Metabolism and nutrition disorders: dehydration, fluid retention, increased appetite, hyperuricemia

Musculoskeletal and connective tissue disorders: myalgia

Nervous system disorders: tremor, sedation, hypoesthesia, paresthesia, disturbance in attention, memory impairment, dysarthria, syncope, balance disorder, dysgeusia, depressed level of consciousness, coordination abnormal, hyperesthesia, myoclonus, dyskinesia, hyperreflexia, encephalopathy, cognitive disorder, convulsion, psychomotor hyperactivity

Psychiatric disorders: confusional state, nervousness, restlessness, abnormal dreams, mood altered, hallucination, panic attack, euphoric mood, paranoia, dysphoria, listless, crying, suicide ideation, libido decreased, aggression

Renal and urinary disorders: dysuria, urinary retention, urinary frequency, urinary hesitation, micturition disorder

Reproductive system and breast disorders: erectile dysfunction, sexual dysfunction

Respiratory, thoracic and mediastinal disorders: rhinorrhea, respiratory distress, hypoxia, bronchospasm, sneezing, hyperventilation, respiratory depression

Skin and subcutaneous tissue disorders: erythema

Vascular disorders: flushing, hypertension, hypotension

6.2 Postmarketing Experience

The following adverse reaction has been identified during post-approval use of EXALGO:
Skin and subcutaneous tissue disorders: urticaria

7 DRUG INTERACTIONS

7.1 CNS Depressants

Avoid use of EXALGO with central nervous system depressants such as hypnotics, sedatives, general anesthetics, antipsychotics and alcohol, due to the increased risk of respiratory depression, hypotension and profound sedation or coma.

7.2 Mixed Agonist/Antagonist Opioid Analgesics

Mixed agonist/antagonists (buprenorphine, nalbuphine, pentazocine) may reduce the analgesic effect of EXALGO and/or may precipitate withdrawal symptoms in these patients. Avoid the use of agonist/antagonist analgesics in patients receiving EXALGO.

7.3 Monoamine Oxidase Inhibitors (MAOI)

The effects of opioid analgesics may be potentiated by MAOIs. EXALGO is not recommended for use in patients who have received MAOIs within 14 days. If concurrent therapy with an MAOI and EXALGO is unavoidable, monitor patients for increased respiratory and central nervous system depression.

7.4 Anticholinergics

Anticholinergics or other medications with anticholinergic activity when used concurrently with EXALGO may result in increased risk of urinary retention and/or severe constipation, which may lead to paralytic ileus. Monitor patients for signs of urinary retention or reduced gastric motility when EXALGO is used concurrently with anticholinergic drugs.

8 USE IN SPECIFIC POPULATIONS

8.1 Pregnancy

Teratogenic Effects

Pregnancy Category C: There are no adequate and well-controlled studies in pregnant women. Hydromorphone crosses the placenta. EXALGO should be used during pregnancy only if the potential benefit justifies the potential risk to the fetus [see Use in Specific Populations (8.2)].

Hydromorphone was not teratogenic in pregnant rats given oral doses up to 6.25 mg/kg/day or in pregnant rabbits administered oral doses up to 25 mg/kg/day during the period of organogenesis (~1.2 times the human exposure following 32 mg/day).

Hydromorphone administration to pregnant Syrian hamsters and CF-1 mice during major organ development revealed teratogenicity likely the result of maternal toxicity associated with sedation and hypoxia. In Syrian hamsters given single subcutaneous doses from 14 to 258 mg/kg during organogenesis (gestation days 8 to 10), doses ≥ 19 mg/kg hydromorphone produced skull malformations (exencephaly and cranioschisis). Continuous infusion of hydromorphone
(5 mg/kg, s.c.) via implanted osmotic mini pumps during organogenesis (gestation days 7 to 10) produced soft tissue malformations (cryptorchidism, cleft palate, malformed ventricals and retina), and skeletal variations (supraoccipital, checkerboard and split sternebrae, delayed ossification of the paws and ectopic ossification sites). The malformations and variations observed in the hamsters and mice were at doses approximately three-fold higher and < one-fold lower, respectively, than a 32 mg human daily oral dose on a body surface area basis.

Nonteratogenic Effects

In the pre- and post-natal effects study in rats, neonatal viability was reduced at 6.25 mg/kg/day (~1.2 times the human exposure following 32 mg/day).

Neonates born to mothers who have been taking opioids regularly prior to delivery will be physically dependent. The withdrawal signs include irritability and excessive crying, tremors, hyperactive reflexes, increased respiratory rate, increased stools, sneezing, yawning, vomiting, and fever. The intensity of the syndrome does not always correlate with the duration of maternal opioid use or dose. There is no consensus on the best method of managing withdrawal. Approaches to the treatment of the syndrome have included supportive care and, if indicated, drugs such as paregoric or phenobarbital.

8.2 Labor and Delivery

EXALGO is not for use in women during and immediately prior to labor, where shorter acting analgesics or other analgesic techniques are more appropriate [see Indications and Usage (1)]. Occasionally, opioid analgesics may prolong labor by temporarily reducing the strength, duration, and frequency of uterine contractions. However, these effects are not consistent and may be offset by an increased rate of cervical dilatation which tends to shorten labor.

Opioids cross the placenta and may produce respiratory depression and psychophysiologic effects in neonates. Closely observe neonates whose mothers received opioid analgesics during labor for signs of respiratory depression. An opioid antagonist, such as naloxone, should be available for reversal of opioid-induced respiratory depression in the neonate in such situations.

8.3 Nursing Mothers

Low concentrations of hydromorphone have been detected in human milk in clinical trials. Withdrawal symptoms can occur in breastfeeding infants when maternal administration of an opioid analgesic is stopped. Nursing should not be undertaken while a patient is receiving EXALGO since hydromorphone is excreted in the milk.

8.4 Pediatric Use

The safety and effectiveness of EXALGO in patients 17 years of age and younger have not been established.

8.5 Geriatric Use

Elderly patients have been shown to be more sensitive to the adverse effects of opioids compared to the younger population. Therefore, closely monitor elderly patients for respiratory and central nervous system depression when prescribing EXALGO, particularly during initiation and titration.

8.6 Neonatal Opioid Withdrawal Syndrome

Chronic maternal use of hydromorphone during pregnancy can affect the neonate with subsequent withdrawal signs. Neonatal withdrawal syndrome presents as irritability, hyperactivity and abnormal sleep pattern, high pitched cry, tremor, vomiting, diarrhea and failure to gain weight. The onset, duration and severity of neonatal withdrawal syndrome vary based on the drug used, duration of use, the dose of last maternal use, and rate of elimination drug by the newborn. Neonatal opioid withdrawal syndrome may be life-threatening and should be treated according to protocols developed by neonatology experts.

8.7 Hepatic Impairment

In a study that used a single 4 mg oral dose of immediate-release hydromorphone tablets, four-fold increases in plasma levels of hydromorphone (Cmax and AUC0-µ) were observed in patients with moderate hepatic impairment (Child-Pugh Group B). Start patients with moderate hepatic impairment on 25% of the EXALGO dose that would be used in patients with normal hepatic function. Closely monitor patients with moderate hepatic impairment for respiratory and central nervous system depression during initiation of therapy with EXALGO and during dose titration. The pharmacokinetics of hydromorphone in severe hepatic impairment patients have not been studied. As further increases in Cmax and AUC0-µ of hydromorphone in this group are expected, use of alternate analgesics is recommended [see Dosage and Administration (2.4)].

8.8 Renal Impairment

Administration of a single 4 mg dose of immediate-release hydromorphone tablets resulted in two-fold and four-fold increases in plasma levels of hydromorphone (Cmax and AUC0-48h) in moderate (CLcr = 40 to 60 mL/min) and severe (CLcr < 30 mL/min) impairment, respectively. In addition, in patients with severe renal impairment hydromorphone appeared to be more slowly eliminated with longer terminal elimination half-life (40 hours) compared to subjects with normal renal function (15 hours). Start patients with moderate renal impairment on 50% and patients with severe renal impairment on 25% of the EXALGO dose that would be prescribed for patients with normal renal function. Closely monitor patients with renal impairment for respiratory and central nervous system depression during initiation of therapy with EXALGO and during dose titration. As EXALGO is only intended for once daily administration, consider use of an alternate analgesic that may permit more flexibility with the dosing interval in patients with severe renal impairment [see Dosage and Administration (2.5)].

9 DRUG ABUSE AND DEPENDENCE

9.1 Controlled Substance

EXALGO contains hydromorphone, a Schedule II controlled substance with a high potential for abuse similar to fentanyl, methadone, morphine, oxycodone, and oxymorphone. EXALGO can be abused and is subject to misuse, abuse, addiction, and criminal diversion [see Warnings and Precautions (5.1)]. The high drug content in the extended release formulation adds to the risk of adverse outcomes from abuse and misuse.

9.2 Abuse

All patients treated with opioids require careful monitoring for signs of abuse and addiction, because use of opioid analgesic products carries the risk of addiction even under appropriate medical use.

Drug abuse is the intentional non-therapeutic use of an over-the-counter or prescription drug, even once, for its rewarding psychological or physiological effects. Drug abuse includes, but is not limited to the following examples: the use of a prescription or over-the-counter drug to get “high”, or the use of steroids for performance enhancement and muscle build up.

Drug addiction is a cluster of behavioral, cognitive, and physiological phenomena that develop after repeated substance use and include: a strong desire to take the drug, difficulties in controlling its use, persisting in its use despite harmful consequences, a higher priority given to drug use than to other activities and obligations, increased tolerance, and sometimes a physical withdrawal.

"Drug-seeking" behavior is very common to addicts and drug abusers. Drug-seeking tactics include emergency calls or visits near the end of office hours, refusal to undergo appropriate examination, testing or referral, repeated claims of loss of prescriptions, tampering with prescriptions and reluctance to provide prior medical records or contact information for other treating physician(s). “Doctor shopping” (visiting multiple prescribers) to obtain additional prescriptions is common among drug abusers, people suffering from untreated addiction and criminals seeking drugs to sell.

Abuse and addiction are separate and distinct from physical dependence and tolerance. Physicians should be aware that addiction may not be accompanied by concurrent tolerance and symptoms of physical dependence in all addicts. In addition, abuse of opioids can occur in the absence of true addiction and is characterized by misuse for non-medical purposes, often in combination with other psychoactive substances.

EXALGO can be diverted for non-medical use into illicit channels of distribution. Careful record-keeping of prescribing information, including quantity, frequency, and renewal requests, as required by law, is strongly advised.

Proper assessment of the patient, proper prescribing practices, periodic re-evaluation of therapy, and proper dispensing and storage are appropriate measures that help to limit abuse of opioid drugs.

Risks Specific to Abuse of EXALGO

EXALGO is intended for oral use only. Abuse of EXALGO poses a risk of overdose and death. This risk is increased with concurrent abuse of EXALGO with alcohol and other substances.

Taking cut, broken, chewed, crushed, or dissolved EXALGO poses a hazard of overdose and death.

With intravenous abuse, the tablet excipients, especially polyethylene oxide, can be expected to result in necrosis and inflammation of cardiac tissues. In addition, parenteral drug abuse is commonly associated with transmission of infectious disease such as hepatitis and HIV.

Healthcare professionals should contact their State Professional Licensing Board or State Controlled Substances Authority for information on how to prevent and detect abuse or diversion of this product.

9.3 Dependence

Both tolerance and physical dependence can develop during chronic opioid therapy. Tolerance is the need for increasing doses of opioids to maintain a defined effect such as analgesia (in the absence of disease progression or other external factors). Tolerance may occur to both the desired and undesired effects of drugs, and may develop at different rates for different effects.

Physical dependence results in withdrawal symptoms after abrupt discontinuation or a significant dose reduction of a drug. Withdrawal also may be precipitated through the administration of drugs with opioid antagonist activity, e.g., naloxone, nalmefene, or mixed agonist/antagonist analgesics (pentazocine, butorphanol, buprenorphine, nalbuphine). Physical dependence may not occur to a clinically significant degree until after several days to weeks of continued opioid usage.

EXALGO should not be abruptly discontinued [see Dosage and Administration (2.3)]. If EXALGO is abruptly discontinued in a physically-dependent patient, an abstinence syndrome may occur. Some or all of the following can characterize this syndrome: restlessness, lacrimation, rhinorrhea, yawning, perspiration, chills, piloerection, myalgia, mydriasis, irritability, anxiety, backache, joint pain, weakness, abdominal cramps, insomnia, nausea, anorexia, vomiting, diarrhea, increased blood pressure, respiratory rate, or heart rate.

Infants born to mothers physically dependent on opioids will also be physically dependent and may exhibit respiratory difficulties and withdrawal symptoms [see Use in Specific Populations (8.1, 8.2)].

10 OVERDOSAGE

Clinical Presentation

Acute overdosage with opioids can be manifested by respiratory depression, somnolence progressing to stupor or coma, skeletal muscle flaccidity, cold and clammy skin, constricted pupils, and sometimes pulmonary edema, bradycardia, hypotension and death. Marked mydriasis rather than miosis may be seen due to severe hypoxia in overdose situations.

Treatment of Overdose

Due to the delayed mean apparent peak plasma level of EXALGO occurring at 16 hours following administration as well as the 11 hour mean elimination half-life of EXALGO, patients who receive an overdose will require an extended period of monitoring and treatment that may go beyond 24 to 48 hours.

In case of overdose, priorities are the re-establishment of a patent and protected airway and institution of assisted or controlled ventilation if needed. Employ other supportive measures (including oxygen, vasopressors) in the management of circulatory shock and pulmonary edema as indicated. Cardiac arrest or arrhythmias will require advanced life support techniques.

The opioid antagonists, such as naloxone and naltrexone, are specific antidotes to respiratory depression resulting from opioid overdose. Opioid antagonists should not be administered in the absence of clinically significant respiratory or circulatory depression secondary to hydromorphone overdose. Such agents should be administered cautiously to patients who are known, or suspected to be, physically dependent on EXALGO. In such cases, an abrupt or complete reversal of opioid effects may precipitate an acute withdrawal syndrome.

Because the duration of reversal would be expected to be less than the duration of action of hydromorphone in EXALGO, carefully monitor the patient until spontaneous respiration is reliably re-established. EXALGO will continue to release hydromorphone adding to the hydromorphone load for up to 24 hours after administration, necessitating prolonged monitoring for at least 24 to 48 hours beyond the overdose. If the response to opioid antagonists is suboptimal or not sustained, additional antagonist should be given as directed in the product’s prescribing information.

In an individual physically dependent on opioids, administration of an opioid receptor antagonist may precipitate an acute withdrawal. The severity of the withdrawal syndrome produced will depend on the degree of physical dependence and the dose of the antagonist administered. If a decision is made to treat serious respiratory depression in the physically dependent patient, administration of the antagonist should be begun with care and by titration with smaller than usual doses of the antagonist.

11 DESCRIPTION

EXALGO tablets are for oral use and contain hydromorphone hydrochloride, a mu-opioid agonist.

Hydromorphone hydrochloride USP is 4,5α-epoxy-3-hydroxy-17-methlymorphinan-6-one hydrochloride. Hydromorphone hydrochloride is a white or almost white crystalline powder that is freely soluble in water, very slightly soluble in ethanol (96%), and practically insoluble in methylene chloride. Its empirical formula is C17H19NO3•HCl. The compound has the following structural formula:

EXALGO also contains the following inactive ingredients: butylated hydroxytoluene, cellulose acetate, iron oxide black, ferric oxide red (8 mg only), ferric oxide yellow (12 mg, 16 mg, and 32 mg only), hypromellose, lactose anhydrous, lactose monohydrate, magnesium stearate, polyethylene glycol, polyethylene oxide, povidone, sodium chloride, titanium dioxide, and triacetin.

12 CLINICAL PHARMACOLOGY

12.1 Mechanism of Action

Hydromorphone, a semi-synthetic morphine derivative, is a hydrogenated ketone of morphine. Hydromorphone is principally an agonist of mu-receptors, showing a weak affinity for k-receptors. Comparing relative binding affinity for mu- and k-opioid receptors, hydromorphone binds more specifically to mu-receptors than structurally related morphine. As an opioid agonist, the principle therapeutic action of hydromorphone is analgesia. The precise mechanism of action of opioid analgesics is not known but the effects are thought to be mediated through opioid-specific receptors located predominantly in the central nervous system (CNS). Interaction with the mu-opioid receptor subtype is believed to be responsible for most of hydromorphone’s clinical effects. There is no intrinsic limit to the analgesic effect of hydromorphone. Clinically, however, dosage limitations are imposed by the adverse effects, primarily respiratory depression, sedation, nausea, and vomiting, which can result from high doses.

12.2 Pharmacodynamics

CNS Depressant/Alcohol Interaction

Additive pharmacodynamic effects may be expected when EXALGO is used in conjunction with alcohol, other opioids, legal or illicit drugs that cause central nervous system depression.

Effects on the Central Nervous System

Hydromorphone produces dose-related respiratory depression by direct action on brain stem respiratory centers. The respiratory depression involves a reduction in the responsiveness of the brain stem respiratory centers to increases in carbon dioxide tension and to electrical stimulation.

Hydromorphone depresses the cough reflex by direct effect on the cough center in the medulla.

Hydromorphone causes miosis, even in total darkness. Pinpoint pupils are a sign of opioid overdose but are not pathognomic. Marked mydriasis, rather than miosis, may be seen due to severe hypoxia in overdose situations.

Effects on the Gastrointestinal Tract and Other Smooth Muscle

Gastric, biliary and pancreatic secretions are decreased by hydromorphone. Hydromorphone causes a reduction in motility associated with an increase in tone in the antrum of the stomach and duodenum. Digestion of food in the small intestine is delayed and propulsive contractions are decreased. Propulsive peristaltic waves in the colon are decreased, while tone may be increased to the point of spasm. The end result is constipation. Hydromorphone also can cause an increase in biliary tract pressure as a result of spasm of the sphincter of Oddi.

Effects on the Cardiovascular System

Hydromorphone produces peripheral vasodilation which may result in orthostatic hypotension or syncope. Release of histamine may be induced by hydromorphone and can contribute to opioid-induced hypotension. Manifestations of histamine release or peripheral vasodilation may include pruritus, flushing, red eyes, and sweating.

Effects on the Endocrine System

Opioids inhibit the secretion of ACTH, cortisol, and luteinizing hormone (LH) in humans. They also stimulate prolactin, growth hormone (GH) secretion, and pancreatic secretion of insulin and glucagon.

Effects on the Immune System

Opioids have been shown to have a variety of effects on components of the immune system in in vitro and animal models. The clinical significance of these findings is unknown. Overall, the effects of opioids appear to be modestly immunosuppressive.

12.3 Pharmacokinetics

Absorption

EXALGO is an extended-release formulation of hydromorphone that produces a gradual increase in hydromorphone concentrations. Following a single-dose administration of EXALGO, plasma concentrations gradually increase over 6 to 8 hours, and thereafter concentrations are sustained for approximately 18 to 24 hours post-dose. The median Tmax values ranged from 12 to 16 hours. The mean half-life was approximately 11 hours, ranging from 8 to 15 hours in most individual subjects. Linear pharmacokinetics has been demonstrated for EXALGO over the dose range 8 to 64 mg, with a dose-proportional increase in Cmax and overall exposure (AUC0-∞) (see Table 4). Steady-state plasma concentrations are approximately twice those observed following the first dose, and steady state is reached after 3 to 4 days of once-daily dosing of EXALGO. At steady state, EXALGO given once daily maintained hydromorphone plasma concentrations within the same concentration range as the immediate-release tablet given 4 times daily at the same total daily dose and diminished the fluctuations between peak and trough concentrations seen with the immediate-release tablet (see Figure 1). The bioavailability of EXALGO once daily and immediate-release hydromorphone four times daily in adults is comparable, as presented in Table 4.

Figure 1.
Mean Steady-State Plasma Concentration Profile

Table 4.
Mean (±SD) EXALGO Pharmacokinetic Parameters

Regimen | Dosage | Tmax* (hrs) | Cmax (ng/mL) | AUC; (ng·hr/mL) | T½ (hr)
Single Dose; (N = 31) | 8 mg | 12 (4-30) | 0.93 (1.01) | 18.1 (5.8) | 10.6 (4.3)
Single Dose; (N = 31) | 16 mg | 16 (6-30) | 1.69 (0.78) | 36.5 (11.3) | 10.3 (2.4)
Single Dose; (N = 31) | 32 mg | 16 (4-24) | 3.25 (1.37) | 72.2 (24.3) | 11.0 (3.2)
Single Dose; (N = 31) | 64 mg | 16 (6-30) | 6.61 (1.75) | 156.0 (30.6) | 10.9 (3.8)
Multiple Dose†; (N = 29) | 16 mg q24h | 12 (6-24) | 3.54 (0.96)‡ | 57.6 (16.3) | NA
Multiple Dose†; (N = 29) | IR 4 mg q6h | 0.75 (0.5-2) | 5.28 (1.37)§ | 54.8 (14.8) | NA

NA = not applicable
*Median (range) reported for Tmax
† Steady-state results on Day 5 (0-24 hours)
‡ Cmin 2.15 (0.87) ng/mL
§ Cmin 1.47 (0.42) ng/mL

Food Effect

The pharmacokinetics of EXALGO are not affected by food as indicated by bioequivalence when administered under fed and fasting conditions. Therefore, EXALGO may be administered without regard to meals. When a 16 mg dose of EXALGO was administered to healthy volunteers immediately following a high-fat meal, the median time to Cmax (Tmax) was minimally affected by the high-fat meal occurring at 16 hours compared to 18 hours while fasting.

Distribution

Following intravenous administration of hydromorphone to healthy volunteers, the mean volume of distribution was 2.9 (±1.3) L/kg, suggesting extensive tissue distribution. The mean extent of binding of hydromorphone to human plasma proteins was determined to be 27% in an in vitro study.

Metabolism

After oral administration of an immediate-release formulation, hydromorphone undergoes extensive first-pass metabolism and is metabolized primarily in the liver by glucuronidation to hydromorphone-3-glucuronide, which follows a similar time course to hydromorphone in plasma. Exposure to the glucuronide metabolite is 35 to 40 times higher than exposure to the parent drug. In vitro data suggest that hydromorphone in clinically relevant concentrations has minimal potential to inhibit the activity of human hepatic CYP450 enzymes including CYP1A2, 2C9, 2C19, 2D6, 3A4, and 4A11.

Excretion

Approximately 75% of the administered dose is excreted in urine. Most of the administered hydromorphone dose is excreted as metabolites. Approximately 7% and 1% of the dose are excreted as unchanged hydromorphone in urine and feces, respectively.

Special Populations
Geriatric Patients

Based on data obtained from a study using immediate-release hydromorphone, the pharmacokinetics of hydromorphone in healthy elderly subjects (65 to 74 years old) are similar to the pharmacokinetics in healthy young subjects.

Pediatric Patients

The pharmacokinetics of EXALGO were not evaluated in a pediatric population.

Gender

Females appeared to have approximately 10% higher mean systemic exposure in terms of Cmax and AUC values.

Race

The effect of race on EXALGO pharmacokinetics has not been studied.

Hepatic Impairment

In a study that used a single 4 mg oral dose of immediate-release hydromorphone tablets, four-fold increases in plasma levels of hydromorphone (Cmax and AUC0-µ) were observed in patients with moderate hepatic impairment (Child-Pugh Group B). Pharmacokinetics of hydromorphone in severe hepatic impairment patients has not been studied. Further increase in Cmax and AUC0-µ of hydromorphone in this group is expected. Start patients with moderate hepatic impairment on 25% of the usual dose of EXALGO and closely monitor for respiratory and central nervous system depression during dose titration. Consider alternate analgesic therapy for patients with severe hepatic impairment [see Dosage and Administration (2.4) and Specific Populations (8.7)].

Renal Impairment

Renal impairment affected the pharmacokinetics of hydromorphone and its metabolites following administration of a single 4 mg dose of immediate-release tablets. The effects of renal impairment on hydromorphone pharmacokinetics were two-fold and four-fold increases in plasma levels of hydromorphone (Cmax and AUC0-48h) in moderate (CLcr = 40 to 60 mL/min) and severe (CLcr < 30 mL/min) impairment, respectively. In addition, in patients with severe renal impairment hydromorphone appeared to be more slowly eliminated with longer terminal elimination half-life (40 hr) compared to subjects with normal renal function (15 hr). Start patients with moderate renal impairment on 50% of the usual EXALGO dose for patients with normal renal function and closely monitor for respiratory and central nervous system depression during dose titration. As EXALGO is only intended for once-daily administration, consider use of an alternate analgesic that may permit more flexibility with the dosing interval in patients with severe renal impairment [see Dosage and Administration (2.5) and Use in Specific Populations (8.8)].

Drug Interaction/Alcohol Interaction

An in vivo study examined the effect of alcohol (40%, 20%, 4% and 0%) on the bioavailability of a single dose of 16 mg of EXALGO in healthy, fasted or fed volunteers. The results showed that the hydromorphone mean AUC0-µ was 5% higher and 4% lower (not statistically significant) in the fasted and fed groups respectively after co-administration of 240 mL of 40% alcohol. The AUC0-µ was similarly unaffected in subjects following the co-administration of EXALGO and alcohol (240 mL of 20% or 4% alcohol).

The change in geometric mean Cmax with concomitant administration of alcohol and EXALGO ranged from an increase of 10% to 31% across all conditions studied. The change in mean Cmax was greater in the fasted group of subjects. Following concomitant administration of 240 mL of 40% alcohol while fasting, the mean Cmax increased by 37% and up to 151% in an individual subject. Following the concomitant administration of 240 mL of 20% alcohol while fasting, the mean Cmax increased by 35% and up to 139% in an individual subject. Following the concomitant administration of 240 mL of 4% alcohol while fasting, the mean Cmax increased by 19% on average and as much as 73% for an individual subject. The range of median Tmax for the fed and fasted treatments with 4%, 20% and 40% alcohol was 12 to 16 hours compared to 16 hours for the 0% alcohol treatments.

13 NONCLINICAL TOXICOLOGY

13.1 Carcinogenesis, Mutagenesis, Impairment of Fertility

Carcinogenesis

Long-term studies in animals to evaluate the carcinogenic potential of hydromorphone hydrochloride have not been conducted.

Mutagenesis

Hydromorphone was not mutagenic in the in vitro bacterial reverse mutation assay (Ames assay). Hydromorphone was not clastogenic in either the in vitro human lymphocyte chromosome aberration assay or the in vivo mouse micronucleus assay.

Impairment of Fertility

Hydromorphone given orally to rats during the mating period caused a slight but statistically significant reduction in implantations at 6.25 mg/kg/day (~1.2 times the human exposure following to 32 mg/day).

14 CLINICAL STUDIES

EXALGO was investigated in a double-blind, placebo-controlled, randomized withdrawal study in opioid tolerant patients with moderate-to-severe low back pain. Patients were considered opioid tolerant if they were currently on opioid therapy that was ≥ 60 mg/day of oral morphine equivalent for at least 2 months prior to screening. Patients entered an open-label conversion and titration phase with EXALGO, were converted to a starting dose that was approximately 75% of their total daily morphine equivalent dose, and were dosed once daily until adequate pain control was achieved while exhibiting tolerable side effects. Supplemental immediate-release hydromorphone tablets were allowed throughout the study. Patients who achieved a stable dose entered a 12-week, double-blind, placebo-controlled, randomized treatment phase. Mean daily dose at randomization was 37.8 mg/day (range of 12 mg/day to 64 mg/day). Fifty-eight (58) percent of patients were successfully titrated to a stable dose of EXALGO during the open-label conversion and titration phase.

During the double-blind treatment phase, patients randomized to EXALGO continued with the stable dose achieved in the conversion and titration phase of the study. Patients randomized to placebo received, in a blinded manner, EXALGO and matching placebo in doses tapering from the stable dose achieved in conversion and titration. During the taper down period, patients were allowed immediate-release hydromorphone tablets as supplemental analgesia to minimize opioid withdrawal symptoms in placebo patients. After the taper period, the number of immediate-release hydromorphone tablets was limited to two tablets per day. Forty-nine (49) percent of patients treated with EXALGO and 33% of patients treated with placebo completed the 12-week treatment period.

EXALGO provided superior analgesia compared to placebo. There was a significant difference between the mean changes from Baseline to Week 12 or Final Visit in average weekly pain intensity Numeric Rating Scale (NRS) scores obtained from patient diaries between the two groups. The proportion of patients with various degrees of improvement from screening to Week 12 or Final Visit is shown in Figure 2. For this analysis, patients who discontinued treatment for any reason prior to Week 12 were assigned a value of zero improvement.

Figure 2.

Percent Reduction in Average Pain Intensity from Screening
to Week 12 or Final Visit

16 HOW SUPPLIED/STORAGE AND HANDLING

How Supplied

EXALGO Tablet Strengths

Strength | Color | Tablet Description | Bottle; Count | NDC
8 mg | Red | Round, biconvex, printed with “EXH 8” | 30 | 54868-6387-0
16 mg | Yellow | Round, biconvex, printed with “EXH 16” | 30 | 54868-6388-0

Store at 25ºC (77ºF); excursions permitted to 15° to 30°C (59° to 86°F) [See USP Controlled Room Temperature].

17 PATIENT COUNSELING INFORMATION

See FDA-approved patient labeling (Medication Guide)

Abuse Potential

Inform patients that EXALGO contains hydromorphone, a Schedule II controlled substance that is subject to abuse. Instruct patients not to share EXALGO with others and to take steps to protect EXALGO from theft or misuse.

Life-threatening Respiratory Depression

Discuss the risk of respiratory depression with patients, explaining that the risk is greatest when starting EXALGO or when the dose is increased. Advise patients how to recognize respiratory depression and to seek medical attention if they are experiencing breathing difficulties.

Accidental Exposure

Instruct patients to take steps to store EXALGO securely. Accidental exposure, especially in children, may result in serious harm or death. Advise patients to dispose of unused EXALGO by flushing the tablets down the toilet or remit to authorities at a certified drug take-back program.

Risks from Concomitant Use of Alcohol and other CNS Depressants

Inform patients that the concomitant use of alcohol with EXALGO can increase the risk of life-threatening respiratory depression. Instruct patients not to consume alcoholic beverages, as well as prescription and over-the-counter drug products that contain alcohol, during treatment with EXALGO.

Inform patients that potentially serious additive effects may occur if EXALGO is used with other CNS depressants, and not to use such drugs unless supervised by a health care provider.

Important Administration Instructions

Instruct patients how to properly take EXALGO, including the following:

- Swallowing EXALGO whole
- Not crushing, chewing, splitting or dissolving the tablets
- Using EXALGO exactly as prescribed to reduce the risk of life-threatening adverse reactions (e.g., respiratory depression)
- Not discontinuing EXALGO without first discussing the need for a tapering regimen with the prescriber

Gastrointestinal Blockage

Advise patients that people with certain stomach or intestinal problems such as narrowing of the intestines or previous surgery may be at higher risk of developing a blockage. Symptoms include abdominal distension, abdominal pain, severe constipation, or vomiting. Instruct patients to contact their healthcare provider immediately if they develop these symptoms.

Hypotension

Inform patients that EXALGO may cause orthostatic hypotension and syncope. Instruct patients how to recognize symptoms of low blood pressure and how to reduce the risk of serious consequences should hypotension occur (e.g., sit or lie down, carefully rise from a sitting or lying position).

Driving or Operating Heavy Machinery

Inform patients that EXALGO may impair the ability to perform potentially hazardous activities such as driving a car or operating heavy machinery. Advise patients not to perform such tasks until they know how they will react to the medication.

Constipation

Advise patients of the potential for severe constipation, including management instructions and when to seek medical attention.

Anaphylaxis

Inform patients that anaphylaxis has been reported with ingredients contained in EXALGO. Advise patients how to recognize such a reaction and when to seek medical attention.

Pregnancy

Advise female patients that EXALGO can cause fetal harm and to inform the prescriber if they are pregnant or plan to become pregnant.

Disposal

Advise patients that when EXALGO is no longer needed to flush the unused tablets down the toilet or remit to authorities at a certified drug take-back program.

EXALGO is a registered trademark of Mallinckrodt LLC.
© 2012 Mallinckrodt LLC

Distributed by:
Mallinckrodt Brand Pharmaceuticals, Inc.
Hazelwood, MO 63042 USA

www.Exalgo.com or call 1-800-778-7898

Mallinckrodt

Distributed by:
Physicians Total Care, Inc.
Tulsa, Oklahoma 74146

Medication Guide

EXALGO® (eks-al-goh)
(hydromorphone hydrochloride) Extended-Release Tablets, CII

EXALGO is:

- A strong prescription pain medicine that contains an opioid (narcotic) that is used to treat moderate to severe around-the-clock pain, in people who are already regularly using opioid pain medicine.

Important information about EXALGO:

- Get emergency help right away if you take too much EXALGO (overdose). EXALGO overdose can cause life threatening breathing problems that can lead to death.
- Never give anyone else your EXALGO. They could die from taking it. Store EXALGO away from children and in a safe place to prevent stealing or abuse. Selling or giving away EXALGO is against the law.

Do not take EXALGO if you have:

- severe asthma, trouble breathing, or other lung problems.
- a bowel blockage or have narrowing of the stomach or intestines.

Before taking EXALGO, tell your healthcare provider if you have a history of:

- head injury, seizures
- liver, kidney, thyroid problems
- allergy to hydromorphone or sulfites
- problems urinating
- pancreas or gallbladder problems
- abuse of street or prescription drugs, alcohol addiction, or mental health problems.

Tell your healthcare provider if you are:

- pregnant or planning to become pregnant. EXALGO may harm your unborn baby.
- breastfeeding. EXALGO passes into breast milk and may harm your baby.
- taking prescription or over-the-counter medicines, vitamins, or herbal supplements.

When taking EXALGO:

- Do not change your dose. Take EXALGO exactly as prescribed by your healthcare provider.
- Take your prescribed dose at the same time every day. Do not take more than your prescribed dose in 24 hours. If you miss a dose, do not take EXALGO. Take your next dose at your usual time the next day.
- Swallow EXALGO whole. Do not cut, break, chew, crush, dissolve, or inject EXALGO.
- Call your healthcare provider if the dose you are taking does not control your pain.
- Do not stop taking EXALGO without talking to your healthcare provider.
- EXALGO is contained in a hard tablet shell that you may see in your bowel movement; this is normal.
- After you stop taking EXALGO, flush any unused tablets down the toilet.

While taking EXALGO Do Not:

- Drive or operate heavy machinery, until you know how EXALGO affects you. EXALGO can make you sleepy, dizzy, or lightheaded.
- Drink alcohol or use prescription or over-the-counter medicines that contain alcohol.

The possible side effects of EXALGO are:

- constipation, nausea, sleepiness, vomiting, tiredness, headache, dizziness. Call your healthcare provider if you have any of these symptoms and they are severe.

Get emergency medical help if you have:

- trouble breathing, shortness of breath, fast heartbeat, chest pain, swelling of your face, tongue or throat, extreme drowsiness, or you are feeling faint.

These are not all the possible side effects of EXALGO. Call your doctor for medical advice about side effects. You may report side effects to FDA at 1-800-FDA-1088. For more information go to dailymed.nlm.nih.gov

EXALGO is a registered trademark of Mallinckrodt LLC.

Distributed by: Mallinckrodt Brand Pharmaceuticals, Inc., Hazelwood, MO 63042 USA, www.Exalgo.com or call 1-800-778-7898

Mallinckrodt

This Medication Guide has been approved by the U.S. Food and Drug Administration. Issue: July 2012 b

PRINCIPAL DISPLAY PANEL - 8 mg

EXALGO® Once Daily
(hydromorphone HCl)
Extended-Release Tablets
CII
8 mg
Rx only
Each tablet contains:
Hydromorphone Hydrochloride USP. . . . . . . 8 mg
For opioid tolerant patients only
Dispense the accompanying Medication
Guide to each patient

PRINCIPAL DISPLAY PANEL - 16 mg

EXALGO® Once Daily
(hydromorphone HCl)
Extended-Release Tablets
CII
16 mg
Rx only
Each tablet contains:
Hydromorphone Hydrochloride USP. . . . . . . 16 mg
For opioid tolerant patients only
Dispense the accompanying Medication
Guide to each patient